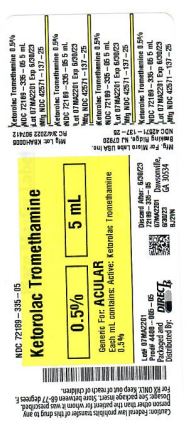 DRUG LABEL: KETOROLAC TROMETHAMINE
NDC: 72189-335 | Form: SOLUTION
Manufacturer: Direct Rx
Category: prescription | Type: HUMAN PRESCRIPTION DRUG LABEL
Date: 20250121

ACTIVE INGREDIENTS: KETOROLAC TROMETHAMINE 5 mg/1 mL
INACTIVE INGREDIENTS: SODIUM CHLORIDE; WATER; BENZALKONIUM CHLORIDE; SODIUM HYDROXIDE; OCTOXYNOL-40; HYDROCHLORIC ACID; EDETATE DISODIUM

Ketorolac Tromethamine

INDICATIONS AND USAGE

Before you use Ketorolac Tromethamine Ophthalmic solution 0.5% for the first time:

1.Check to make sure that the tamper evident ring between the bottle and the cap is not broken (See Figure A). If the tamper evident ring is broken or missing, contact your pharmacist.

[Img-fig-a]

2.Tear off the tamper evident ring (See Figure B).

[Img-fig-b]

3.To open the bottle, remove the cap by turning it in the counterclockwise direction (See Figure C).

[Img-fig-c]

This Instructions for Use has been approved by the U.S. Food and Drug Administration.

Rev.10/2021

PATIENT COUNSELING INFORMATION

17.1 Slow or Delayed Healing

Patients should be informed of the possibility that slow or delayed healing may occur while using nonsteroidal anti-inflammatory drugs (NSAIDs).

17.2 Avoiding Contamination of the Product

Patients should be instructed to avoid allowing the tip of the bottle to contact the eye or surrounding structures because this could cause the tip to become contaminated by common bacteria known to cause ocular infections. Serious damage to the eye and subsequent loss of vision may result from using contaminated solutions.

Also, to avoid the potential for cross-contamination, the patient should be advised to use one bottle for each eye following bilateral ocular surgery. The use of the same bottle of topical eye drops for both eyes following bilateral ocular surgery is not recommended.

17.3 Contact Lens Wear

Patients should be advised that ketorolac tromethamine ophthalmic solution 0.5% should not be administered while wearing contact lenses.

17.4 Intercurrent Ocular Conditions

Patients should be advised that if they develop an intercurrent ocular condition (e.g., trauma or infection) or have ocular surgery, they should immediately seek their physician’s advice concerning the continued use of ketorolac tromethamine ophthalmic solution 0.5%.

17.5 Concomitant Topical Ocular Therapy

Patients should be advised that if more than one topical ophthalmic medication is being used, the medicines should be administered at least 5 minutes apart.

Manufactured by:

Micro Labs Limited

Bangalore-560099, INDIA.

Manufactured for:

Micro Labs USA Inc.

Somerset, NJ 08873

Rev.10/2021

HOW SUPPLIED

Ketorolac Tromethamine Ophthalmic solution 0.5% is supplied sterile, in white opaque LDPE bottles with white opaque LDPE Nozzles with HDPE grey caps as follows.

3 mL in 5 mL bottle NDC 42571-137-31

5 mL in 5 mL bottle NDC 42571-137-25

10 mL in 10 mL bottle NDC 42571-137-26

Storage: Store at 20° to 25°C (68° to 77°F) [see USP Controlled Room Temperature].

CLINICAL STUDIES

Two controlled clinical studies showed that ketorolac tromethamine ophthalmic solution was significantly more effective than its vehicle in relieving ocular itching caused by seasonal allergic conjunctivitis.

Two controlled clinical studies showed that patients treated for two weeks with ketorolac tromethamine ophthalmic solution were less likely to have measurable signs of inflammation (cell and flare) than patients treated with its vehicle.

Results from clinical studies indicate that ketorolac tromethamine has no significant effect upon intraocular pressure; however, changes in intraocular pressure may occur following cataract surgery.

DESCRIPTION

Ketorolac tromethamine ophthalmic solution 0.5% is a member of the pyrrolo-pyrrole group of nonsteroidal anti-inflammatory drugs (NSAIDs) for ophthalmic use. Its chemical name is (±)-5-Benzoyl-2,3-dihydro-1H pyrrolizine-1-carboxylic acid compound with 2-amino-2-(hydroxymethyl)-1,3-propanediol (1:1) and it has the following structure:

Ketorolac tromethamine ophthalmic solution 0.5% is supplied as a sterile isotonic aqueous 0.5% solution, with a pH of 7.4. Ketorolac tromethamine ophthalmic solution 0.5% is a racemic mixture of R-(+) and S-(-)- ketorolac tromethamine. Ketorolac tromethamine may exist in three crystal forms. All forms are equally soluble in water. The pKa of ketorolac is 3.5. This white to off-white crystalline substance discolors on prolonged exposure to light. The molecular weight of ketorolac tromethamine is 376.41. The osmolality of ketorolac tromethamine ophthalmic solution 0.5% is 290 mOsmol/kg.

Each mL of ketorolac tromethamine ophthalmic solution contains: Active: ketorolac tromethamine 0.5%. Preservative: benzalkonium chloride 0.01%. Inactives: edetate disodium 0.1%; octoxynol 40; water for injection; sodium chloride; hydrochloric acid and/or sodium hydroxide to adjust the pH.

INDICATIONS AND USAGE

Ketorolac tromethamine ophthalmic solution 0.5% is indicated for the temporary relief of ocular itching due to seasonal allergic conjunctivitis. Ketorolac tromethamine ophthalmic solution 0.5% is also indicated for the treatment of postoperative inflammation in patients who have undergone cataract extraction.